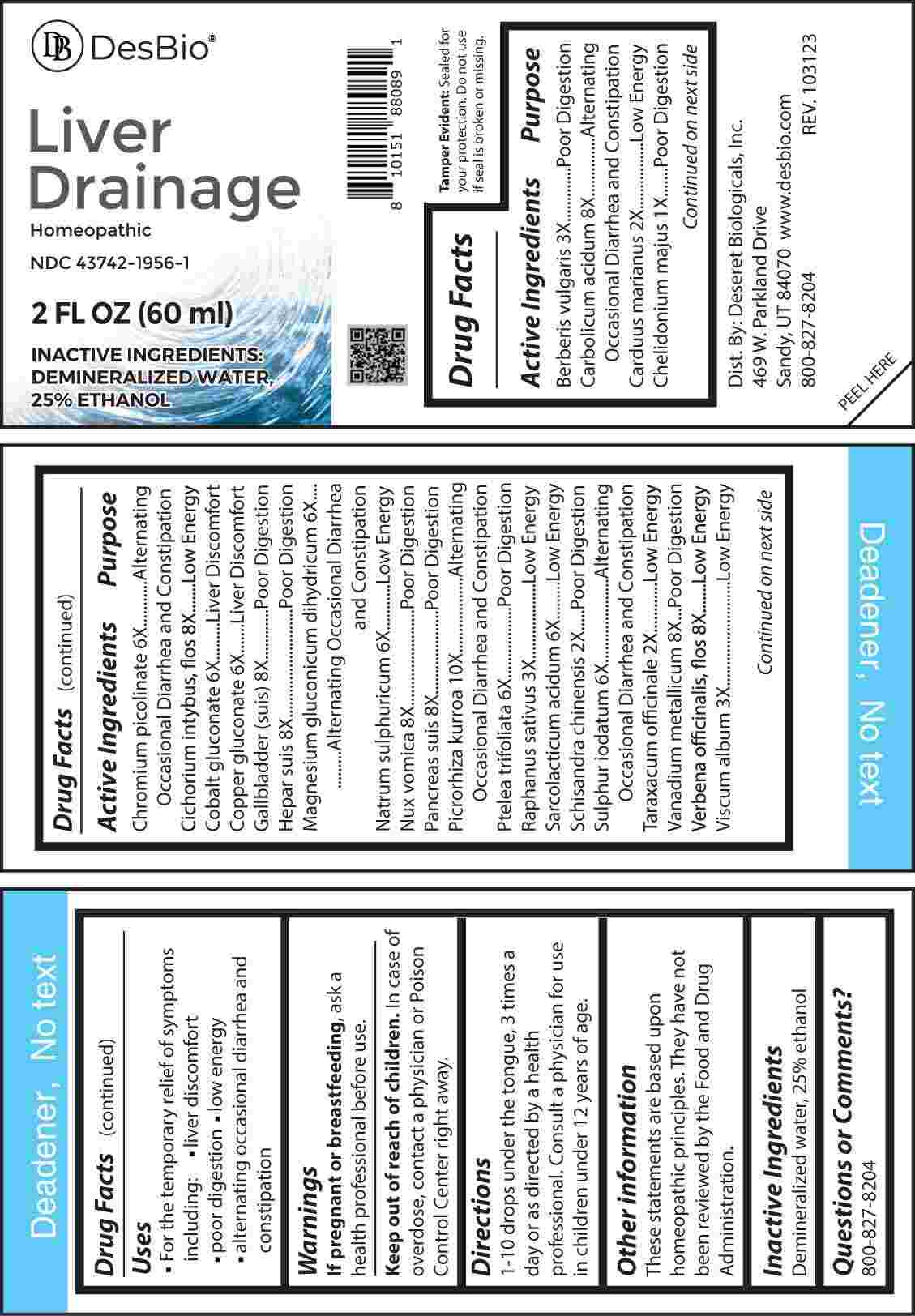 DRUG LABEL: Liver Drainage
NDC: 43742-1956 | Form: LIQUID
Manufacturer: Deseret Biologicals, Inc.
Category: homeopathic | Type: HUMAN OTC DRUG LABEL
Date: 20240529

ACTIVE INGREDIENTS: CHELIDONIUM MAJUS WHOLE 1 [hp_X]/1 mL; MILK THISTLE 2 [hp_X]/1 mL; SCHISANDRA CHINENSIS FRUIT 2 [hp_X]/1 mL; TARAXACUM OFFICINALE 2 [hp_X]/1 mL; BERBERIS VULGARIS ROOT BARK 3 [hp_X]/1 mL; RADISH 3 [hp_X]/1 mL; VISCUM ALBUM FRUITING TOP 3 [hp_X]/1 mL; CHROMIUM PICOLINATE 6 [hp_X]/1 mL; COBALTOUS GLUCONATE 6 [hp_X]/1 mL; COPPER GLUCONATE 6 [hp_X]/1 mL; MAGNESIUM GLUCONATE 6 [hp_X]/1 mL; SODIUM SULFATE 6 [hp_X]/1 mL; PTELEA TRIFOLIATA BARK 6 [hp_X]/1 mL; LACTIC ACID, L- 6 [hp_X]/1 mL; SULFUR IODIDE 6 [hp_X]/1 mL; PHENOL 8 [hp_X]/1 mL; CICHORIUM INTYBUS FLOWER 8 [hp_X]/1 mL; SUS SCROFA GALLBLADDER 8 [hp_X]/1 mL; PORK LIVER 8 [hp_X]/1 mL; STRYCHNOS NUX-VOMICA SEED 8 [hp_X]/1 mL; SUS SCROFA PANCREAS 8 [hp_X]/1 mL; VANADIUM 8 [hp_X]/1 mL; VERBENA OFFICINALIS FLOWERING TOP 8 [hp_X]/1 mL; PICRORHIZA KURROA WHOLE 10 [hp_X]/1 mL
INACTIVE INGREDIENTS: WATER; ALCOHOL

DRUG FACTS:

ACTIVE INGREDIENTS:

Berberis Vulgaris 3X, Carbolicum Acidum 8X, Carduus Marianus 2X, Chelidonium Majus 1X, Chromium Picolinate 6X, Cichorium Intybus, Flos 8X, Cobalt Gluconate 6X, Copper Gluconate 6X, Gallbladder (Suis) 8X, Hepar Suis 8X, Magnesium Gluconate Dihydricum 6X, Natrum Sulphuricum 6X, Nux Vomica 8X, Pancreas Suis 8X, Picrorhiza Kurroa 10X, Ptelea Trifoliata 6X, Raphanus Sativus 3X, Sarcolacticum Acidum 6X, Schisandra Chinensis 2X, Sulphur Iodatum 6X, Taraxacum Officinale 2X, Vanadium Metallicum 8X, Verbena Officinalis, Flos 8X, Viscum Album 3X.

PURPOSE:

Berberis Vulgaris – Poor Digestion, Carbolicum Acidum – Alternating Occasional Diarrhea and Constipation, Carduus Marianus – Low Energy, Chelidonium Majus – Poor Digestion, Chromium Picolinate - Alternating Occasional Diarrhea and Constipation, Cichorium Intybus, Flos – Low Energy, Cobalt Gluconate – Liver Discomfort, Copper Gluconate – Liver Discomfort, Gallbladder (Suis) – Poor Digestion, Hepar Suis – Poor Digestion, Magnesium Gluconate Dihydricum – Alternating Occasional Diarrhea and Constipation, Natrum Sulphuricum – Low Energy, Nux Vomica – Poor Digestion, Pancreas Suis – Poor Digestion, Picrorhiza Kurroa- Alternating Occasional Diarrhea and Constipation, Ptelea Trifoliata – Poor Digestion, Raphanus Sativus – Low Energy, Sarcolacticum Acidum – Low Energy, Schisandra Chinensis – Poor Digestion, Sulphur Iodatum - Alternating Occasional Diarrhea and Constipation, Taraxacum Officinale – Low Energy, Vanadium Metallicum – Poor Digestion, Verbena Officinalis, Flos – Low Energy, Viscum Album – Low Energy

USES:

• For the temporary relief of symptoms including:

• liver discomfort • poor digestion • low energy

• alternating occasional diarrhea and constipation

These statements are based upon homeopathic practices. They have not been reviewed by the Food and Drug Administration.

WARNINGS:

If pregnant or breast-feeding, ask a health professional before use.

Keep out of reach of children. In case of overdose, contact a physician or Poison Control Center right away.

Tamper Evident: Sealed for your protection. Do not use if seal is broken or missing.

KEEP OUT OF REACH OF CHILDREN:

In case of overdose, contact a physician or Poison Control Center right away.

DIRECTIONS:

1-10 drops under the tongue, 3 times a day or as directed by a health professional. Consult a physician for use in children under 12 years of age.

INACTIVE INGREDIENTS:

Demineralized water, 25% ethanol

QUESTIONS:

Dist. By: Deseret Biologicals, Inc.

469 W. Parkland Drive

Sandy, UT 84070

www.desbio.com

800-827-8204

PACKAGE LABEL DISPLAY:

Des Bio

Liver Drainage

Homeopathic

NDC 43742-1956-1

2 FL OZ (60 ml)